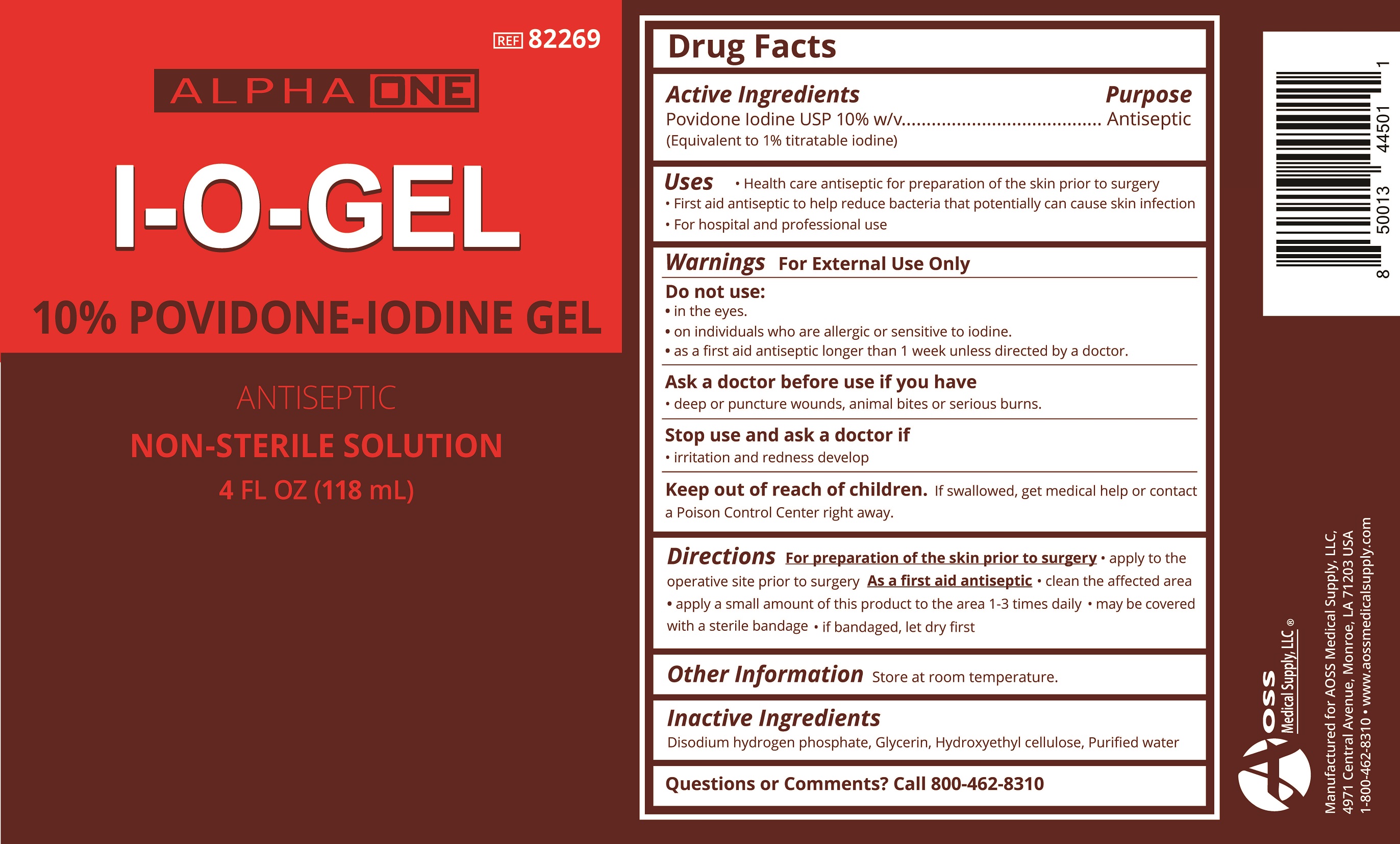 DRUG LABEL: ALPHA ONE
NDC: 53152-2004 | Form: GEL
Manufacturer: AOSS Medical Supply, Inc.
Category: otc | Type: HUMAN OTC DRUG LABEL
Date: 20191023

ACTIVE INGREDIENTS: POVIDONE-IODINE 10 mg/1 mL
INACTIVE INGREDIENTS: HYDROXYETHYL CELLULOSE (2000 CPS AT 1%); SODIUM PHOSPHATE, DIBASIC, ANHYDROUS; WATER; GLYCERIN

Active Ingredients:
Povidone-iodine USP 10% w/v

Purpose

Antiseptic

Uses

- Health care antiseptic for preparation of the skin prior to surgery
- First aid antiseptic to help reducce bacteria that potentially can cause skin infection
- For hospital and professional use

Warnings For external use only.

Do not use:

- in the eyes.
- on individuals who are allergic or sensitive to iodine
- as a first aid antiseptic longer than 1 week unless directed by a doctor.

Ask a doctor before use if you have

- deep or puncture wounds, animal bites or serious burns.

Stop use and ask a doctor if

- irritation or redness develop

Keep out of reach of children. If swallowed, get medical help or contact a Poison Control Center right away.

Directions

For preparation of the skin prior to surgery

- apply to the operative site prior to surgery

As a first aid antiseptic

- clean the affected area
- apply a small amount of this product to the area 1-3 times daily
- may be covered with a sterile bandage
- if bandaged, let dry first

Inactive Ingredients

Disodium hydrogen phosphate, Glycerin, Hydroxyethyl cellulose, Purified water

Other Information

Store at room temperature.